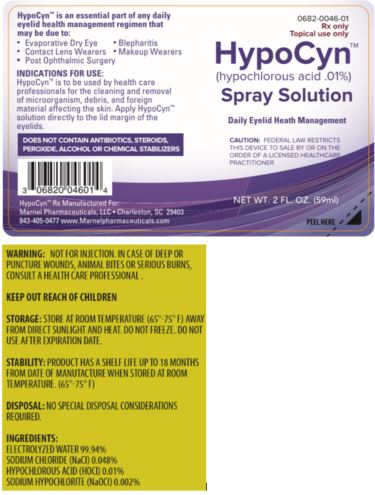 DRUG LABEL: HypoCyn
NDC: 0682-0046
Manufacturer: Marnel Pharmaceuticals, Inc.
Category: other | Type: PRESCRIPTION MEDICAL DEVICE LABEL
Date: 20180913

HypoCyn™
(hypochlorous acid .01%)

INDICATIONS AND USAGE

Rx Only

Topical Use Only

Spray Solution

DAILY EYELID HEALTH MANAGEMENT

INDICATIONS FOR USE: HypoCyn™ is to be used by health care professionals for the cleaning and removal of microorganism, debris, and foreign material affecting the skin.

Apply HypoCyn™ solution directly to the lid margin of the eyelid.

HOW SUPPLIED

HOW SUPPLIED: one 2-ounce bottle with spray applicator.

DIRECTIONS OF USE:

Twice Daily - In the morning and in the evening

1. Wash hands prior to application.

2. Remove any makeup or lotions around your eyes.

3. Close your eye.

4. Apply 1 or 2 sprays directly to the eyelids.

5. Remove excess with a clean cloth if necessary.

6. Repeat on other eye.

7. Use twice daily

STORAGE AND HANDLING

STORAGE: Store at room temperature (65ο to 75ο F) away from direct sunlight and heat. Do not freeze. HypoCyn™is non-flammable.

HANDLING: Non-cytotoxic, non-sensitizing and non-irritating to the skin and eyes. Harmless to common surfaces. No special handling precautions required.

WARNINGS AND PRECAUTIONS: For external use only. Do not use for infusion or injection. Do not swallow. If you experience redness, swelling, irritation or pain, discontinue use and contact your doctor. In case of sensitivities to chlorine, please exercise caution and consult with your doctor prior to use. Do not use expired product.